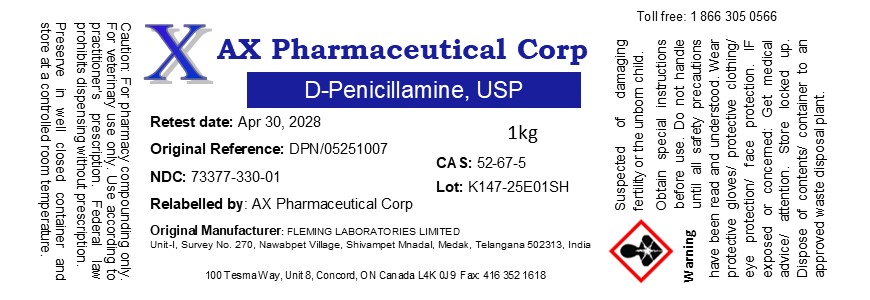 DRUG LABEL: D-Penicillamine
NDC: 73377-330 | Form: POWDER
Manufacturer: AX Pharmaceutical Corp
Category: other | Type: BULK INGREDIENT - ANIMAL DRUG
Date: 20250814

ACTIVE INGREDIENTS: PENICILLAMINE 1 g/1 g

D-Penicillamine